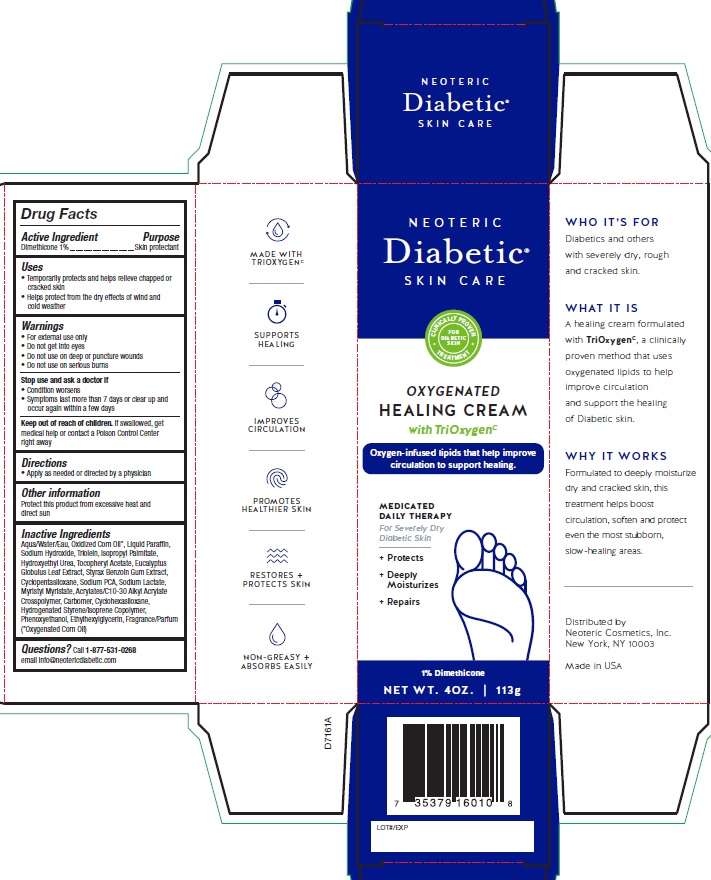 DRUG LABEL: Diabetic Advanced Healing Cream
NDC: 62673-161 | Form: CREAM
Manufacturer: Neoteric Cosmetics, Inc.
Category: otc | Type: HUMAN OTC DRUG LABEL
Date: 20250430

ACTIVE INGREDIENTS: DIMETHICONE 0.01 mg/1 g
INACTIVE INGREDIENTS: WATER; CORN OIL; MINERAL OIL; SODIUM HYDROXIDE; ISOPROPYL PALMITATE; SODIUM LACTATE; ALPHA-TOCOPHEROL ACETATE; CYCLOMETHICONE; SODIUM PYRROLIDONE CARBOXYLATE; EUCALYPTUS GLOBULUS LEAF; MYRISTYL MYRISTATE; TRIOLEIN; HYDROXYETHYL UREA; CARBOMER INTERPOLYMER TYPE A (55000 CPS); STYRAX BENZOIN GUM; CYCLOHEXASILOXANE; STYRENE/ISOPRENE COPOLYMER (28:72; 210000 MW); PHENOXYETHANOL; ETHYLHEXYLGLYCERIN; CARBOMER COPOLYMER TYPE B (ALLYL PENTAERYTHRITOL CROSSLINKED)

Diabetic Advanced Healing Cream

Drug Facts

Active ingredient

Dimethicone 1%

Purpose

Skin protection

Uses

- Temporarily protects and helps relieve chapped or cracked skin
- Helps protect from the dry effects of wind and cold weather

Warnings

- For external use only.
- Do not get into eyes
- Do not use on deep or puncture wounds
- Do not use on serious burns

Stop use and ask a doctor if

- Condition worsens
- Symptoms last more than 7 days or clear up and occur again within a few days

Keep out of reach of children

If swallowed, get medical help or contact a Poison Control Center right away

Directions

- Apply as needed or directed by a physician

Inactive ingredients

Aqua/Water/Eau, Oxidized Corn Oil*, Liquid Paraffin, Sodium Hydroxide, Triolein, Isopropyl Palmitate, Hydroxyethyl Urea, Tocopheryl Acetate, Eucalyptus Globulus Leaf Extract, Styrax Benzoin Gum Extract, Cyclopentasiloxane, Sodium PCA, Sodium Lactate, Myristyl Myristate, Acrylates/C10-30 Alkyl Acrylate Crosspolymer, Carbomer, Cyclohexasiloxane, Hydrogenated Styrene/Isoprene Copolymer, Phenoxyethanol, Ethylhexylglycerin, Fragrance/Parfum (*Oxygenated Corn Oil)

Questions?

Call 1-877-531-0268

email info@neotericdiabetic.com

Distributed by

Neoteric Cosmetics, Inc.

New York, NY 10003

Made in USA

PACKAGE LABEL

NEOTERIC

Diabetic®
SKIN CARE

CLINICALLY PROVEN TREATMENT FOR DIABETIC SKIN

OXYGENATED

HEALING CREAM

with TriOxygenc

Oxygen-infused lipids that help improve circulation to support healing.

MEDICATED DAILY THERAPY

For Severely Dry Diabetic Skin

+ Protects

+ Deeply Moisturizes

+ Repairs

1% Dimethicone

NET WT 4OZ | 113G